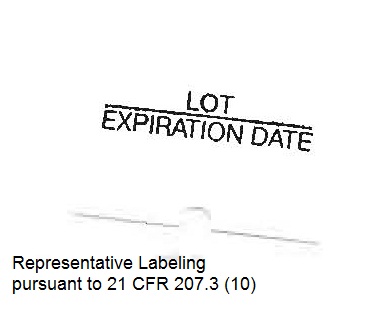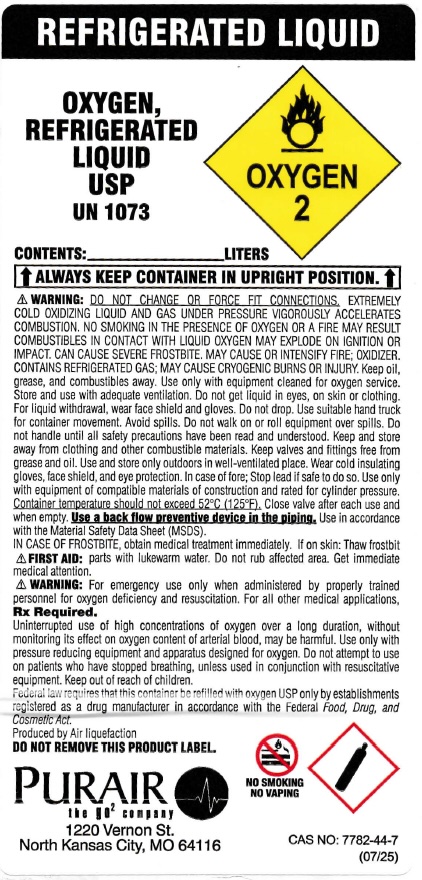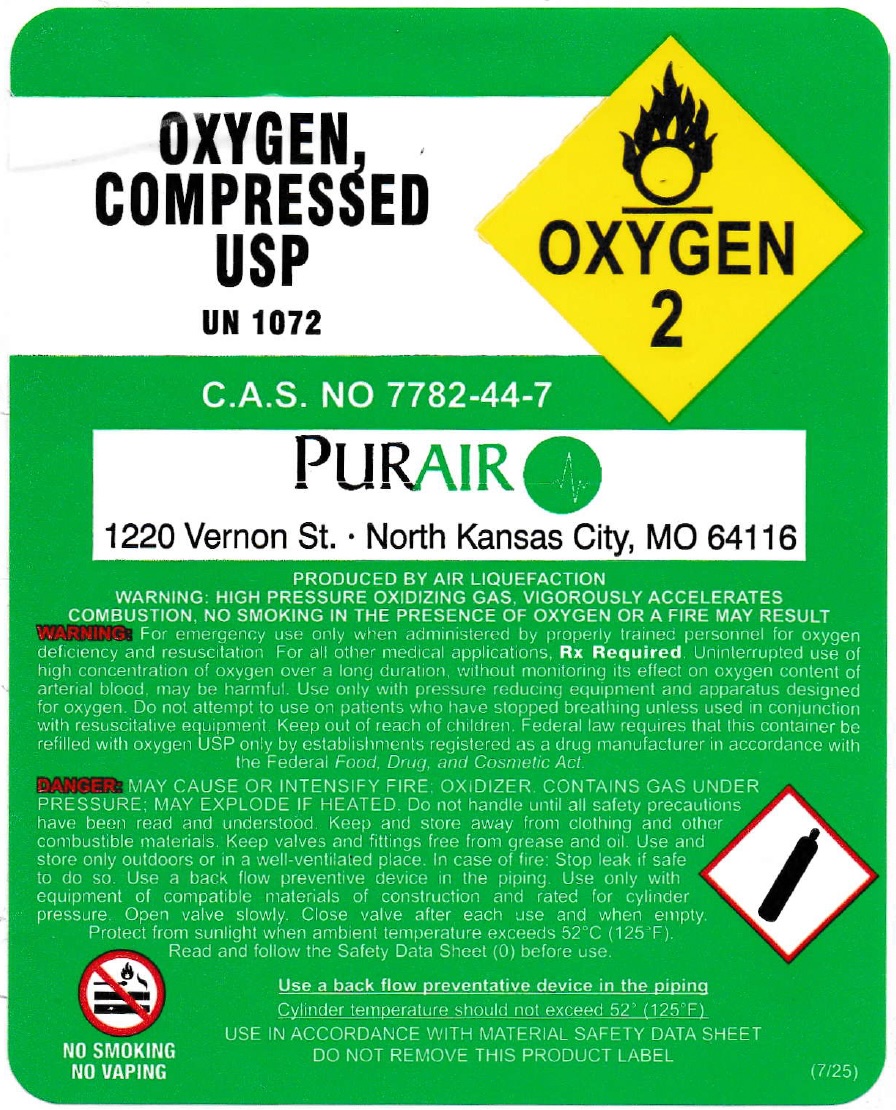 DRUG LABEL: Oxygen
NDC: 72660-001 | Form: GAS
Manufacturer: Medical Equipment Solutions Inc dba Pur Air Products
Category: prescription | Type: HUMAN PRESCRIPTION DRUG LABEL
Date: 20251023

ACTIVE INGREDIENTS: OXYGEN 99 L/100 L

Oxygen, USP

Principal for Oxygen Product

OXYGEN, COMPRESSED USP
UN 1072

C.A.S. NO 7782-44-7

PurAIR
1220 Vernon St. · North Kansas City, MO 64116

PRODUCED BY AIR LIQUEFACTION
WARNING: HIGH PRESSURE OXIDIZING GAS, VIGOROUSLY ACCELERATES COMBUSTION, NO SMOKING IN THE PRESENCE OF OXYGEN OR A FIRE MAY RESULT

WARNING: For emergency use only when administered by properly trained personnel for oxygen deficiency and resuscitation. For all other medical applications, Rx Required. Uninterrupted use of high concentration of oxygen over a long duration, without monitoring its effect on oxygen content of arterial blood, may be harmful. Use only with pressure reducing equipment and apparatus designed for oxygen. Do not attempt to use on patients who have stopped breathing unless used in conjunction with resuscitative equipment. Keep out of reach of children. Federal law requires that this container be refilled with oxygen USP only by establishments registered as a drug manufacturer in accordance with the Federal Food, Drug, and Cosmetic Act.

DANGER: MAY CAUSE OR INTENSIFY FIRE; OXIDIZER. CONTAINS GAS UNDER PRESSURE; MAY EXPLODE IF HEATED. Do not handle until all safety precautions have been read and understood. Keep and store away from clothing and other combustible materials. Keep valves and fittings free from grease and oil. Use and store only outdoors or in a well-ventilated place. In case of fire: Stop leak if safe to do so. Use a back flow preventative device in the piping. Use only with equipment of compatible materials of construction and rated for cylinder pressure. Open valve slowly. Close valve after each use and when empty. Protect from sunlight when ambient temperature exceeds 52°C (125°F).

Read and follow the Safety Data Sheet (SDS) before use.

Use a back flow preventative device in the piping
Cylinder temperature should not exceed 52°C (125°F)

USE IN ACCORDANCE WITH MATERIAL SAFETY DATA SHEET
DO NOT REMOVE THIS PRODUCT LABEL

NO SMOKING
NO VAPING

(7/25)

REFRIGERATED LIQUID

OXYGEN, REFRIGERATED LIQUID USP
UN 1073

CONTENTS: ___________ LITERS

⬆ ALWAYS KEEP CONTAINER IN UPRIGHT POSITION. ⬆

WARNING: DO NOT CHANGE OR FORCE FIT CONNECTIONS. EXTREMELY COLD OXIDIZING LIQUID AND GAS UNDER PRESSURE VIGOROUSLY ACCELERATES COMBUSTION. NO SMOKING IN THE PRESENCE OF OXYGEN OR A FIRE MAY RESULT.
COMBUSTIBLES IN CONTACT WITH LIQUID OXYGEN MAY EXPLODE ON IGNITION OR IMPACT. CAN CAUSE SEVERE FROSTBITE. MAY CAUSE OR INTENSIFY FIRE; OXIDIZER. CONTAINS REFRIGERATED GAS; MAY CAUSE CRYOGENIC BURNS OR INJURY. KEEP OIL, GREASE, AND COMBUSTIBLES AWAY. Use only with equipment cleaned for oxygen service. Store and use with adequate ventilation. Do not get liquid in eyes, on skin or clothing. For liquid withdrawal, wear face shield and gloves. Do not drop. Use suitable hand truck for container movement. Avoid spills. Do not roll or slide. Close valve after each use and when empty. Use a back flow preventative device in the piping. Use in accordance with the Material Safety Data Sheet (MSDS).

Cylinder temperature should not exceed 52°C (125°F).

Close valve after each use and when empty. Use a back flow preventative device in the piping. Use in accordance with the Material Safety Data Sheet (MSDS).

IN CASE OF FROSTBITE, obtain medical treatment immediately. If on skin: Thaw frosted parts with lukewarm water. Do not rub affected area. Get immediate medical attention.

WARNING: For emergency use only when administered by properly trained personnel for oxygen deficiency and resuscitation. For all other medical applications, Rx Required.

Uninterrupted use of high concentrations of oxygen over a long duration, without monitoring its effect on oxygen content of arterial blood, may be harmful. Use only with pressure reducing equipment and apparatus designed for oxygen. Do not attempt to use on patients who have stopped breathing unless used in conjunction with resuscitative equipment. Keep out of reach of children.

Federal law requires that this container be refilled with oxygen USP only by establishments registered as a drug manufacturer in accordance with the Federal Food, Drug, and Cosmetic Act.

Produced by Air liquefaction

DO NOT REMOVE THIS PRODUCT LABEL

PurAIR
the go₂ company
1220 Vernon St.
North Kansas City, MO 64116

NO SMOKING
NO VAPING

CAS NO: 7782-44-7
(07/25)